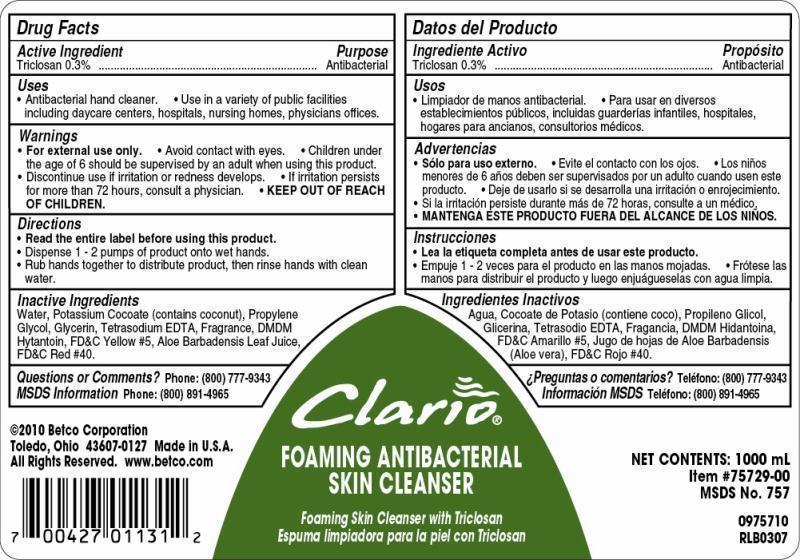 DRUG LABEL: Clario Foaming Antibacterial Skin Cleanser
NDC: 65601-757 | Form: SOAP
Manufacturer: Betco Corporation, Ltd.
Category: otc | Type: HUMAN OTC DRUG LABEL
Date: 20121204

ACTIVE INGREDIENTS: TRICLOSAN 3.0 mg/1 mL
INACTIVE INGREDIENTS: WATER; POTASSIUM COCOATE; PROPYLENE GLYCOL; GLYCERIN; EDETATE SODIUM; DMDM HYDANTOIN; FD&C YELLOW NO. 5; ALOE VERA Leaf; FD&C RED NO. 40

Clario Foaming Antibacterial Skin Cleanser

Clario Foaming Antibacterial Skin Cleanser

Active Ingredient

Triclosan 0.30%

Clario Foaming Antibacterial Skin Cleanser

Uses

- Antibacterial hand cleaner.
- Use in a variet of public facilities including daycare centers, hospitals, nursing homes, physicians offices.

Clario Foaming Antibacterial Skin Cleanser

Warnings

- For external use only.
- Avoid contact with eyes.
- Children under the age of 6 should be supervised by an adult when using this product.
- Discontinue use is irritation or redness develops.
- If irritation persists for more than 72 hours, consult a physician.
- KEEP OUT OF REACH OF CHILDREN.

Clario Foaming Antibacterial Skin Cleanser

Directions

- Read the entire label before using this product.
- Dispense 0.8 mL of product onto wet palm.
- Rub hands together to distribute product, then rinse hands with clean.

Clario Foaming Antibacterial Skin Cleanser

Inactive Ingredients

Water, Potasium cocoate (contains coconut), Propylene Glycol, Glycerine, DMDM Hydantoin, Fragrance, FD&C Yellow #5, Aloe Barbadensis Leaf Juice. FD&C Red #40.

Clario Foaming Antibacterial Skin Cleanser

Questions or Comments? Phone: (800) 777-9343

MDS information:(800) 891-4965

Clario Foaming Antibacterial Skin Cleanser

Purpose

Antibacterial

Clario Foaming Antibacterial Skin Cleanser

KEEP OUT OF REACH OF CHILDREN

Clario Foaming Antibacterial Skin Cleanser

Foaming Skin Cleanser with Triclosan

NET CONTENTS: 1000 L

Item Number 75729-00

MSDS No. 757

0975710

RLB0307

2010 Betco Corporation

Toledo, Ohio 43607-0127 Made in USA

All Rights Reserved. www.betco.com